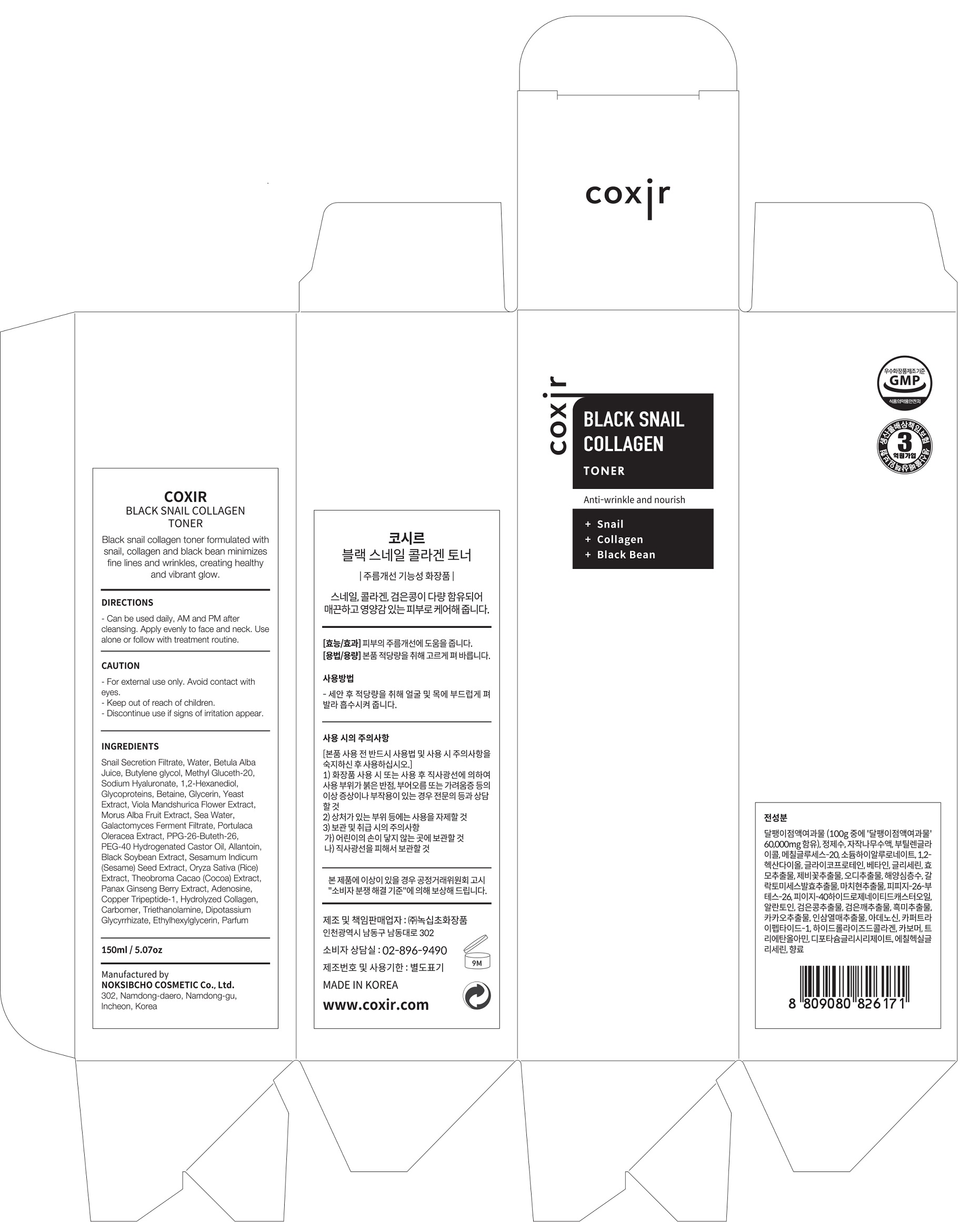 DRUG LABEL: Black Snail Collagen Toner
NDC: 73590-0014 | Form: LIQUID
Manufacturer: NOKSIBCHO cosmetic Co., Ltd.
Category: otc | Type: HUMAN OTC DRUG LABEL
Date: 20200314

ACTIVE INGREDIENTS: SNAIL, UNSPECIFIED 60 g/100 mL
INACTIVE INGREDIENTS: WATER; BUTYLENE GLYCOL

Drug Facts

ACTIVE INGREDIENT

Snail Secretion Filtrate

INACTIVE INGREDIENT

Water
Betula Alba Juice
Butylene glycol
Methyl Gluceth-20
Sodium Hyaluronate
1,2-Hexanediol
Water
Glycoproteins
Sodium Hyaluronate
Betaine
Butylene glycol
Glycerin
1,2-Hexanediol
Viola Mandshurica Flower Extract
Morus Alba Fruit Extract
Sea Water
Galactomyces Ferment Filtrate
Portulaca Oleracea Extract
PPG-26-Buteth-26
PEG-40 Hydrogenated Castor Oil
Allantoin
Black Soybean Extract
Sesamum Indicum (Sesame)
Seed Extract
Oryza Sativa (Rice) Extract
Theobroma Cacao (Cocoa) Extract
Panax Ginseng Berry Extract
Adenosine
Copper Tripeptide-1
Hydrolyzed Collagen
Carbomer
Triethanolamine
Dipotassium Glycyrrhizate
Ethylhexylglycerin
Parfum

PURPOSE

anti-wrinkle and nourish

keep out of reach of the children

INDICATIONS AND USAGE

apply proper amount and gently massage

WARNINGS

For external use only
When using this product

■ if the following symptoms occurs after use, stop use and consult with a skin specialist

red specks, swelling, itching

■ don’t use on the part where there is injury, eczema, or dermatitis

Keep out of reach of children

■ if swallowed, get medical help or contact a person control center immediately

DOSAGE AND ADMINISTRATION

for external use only